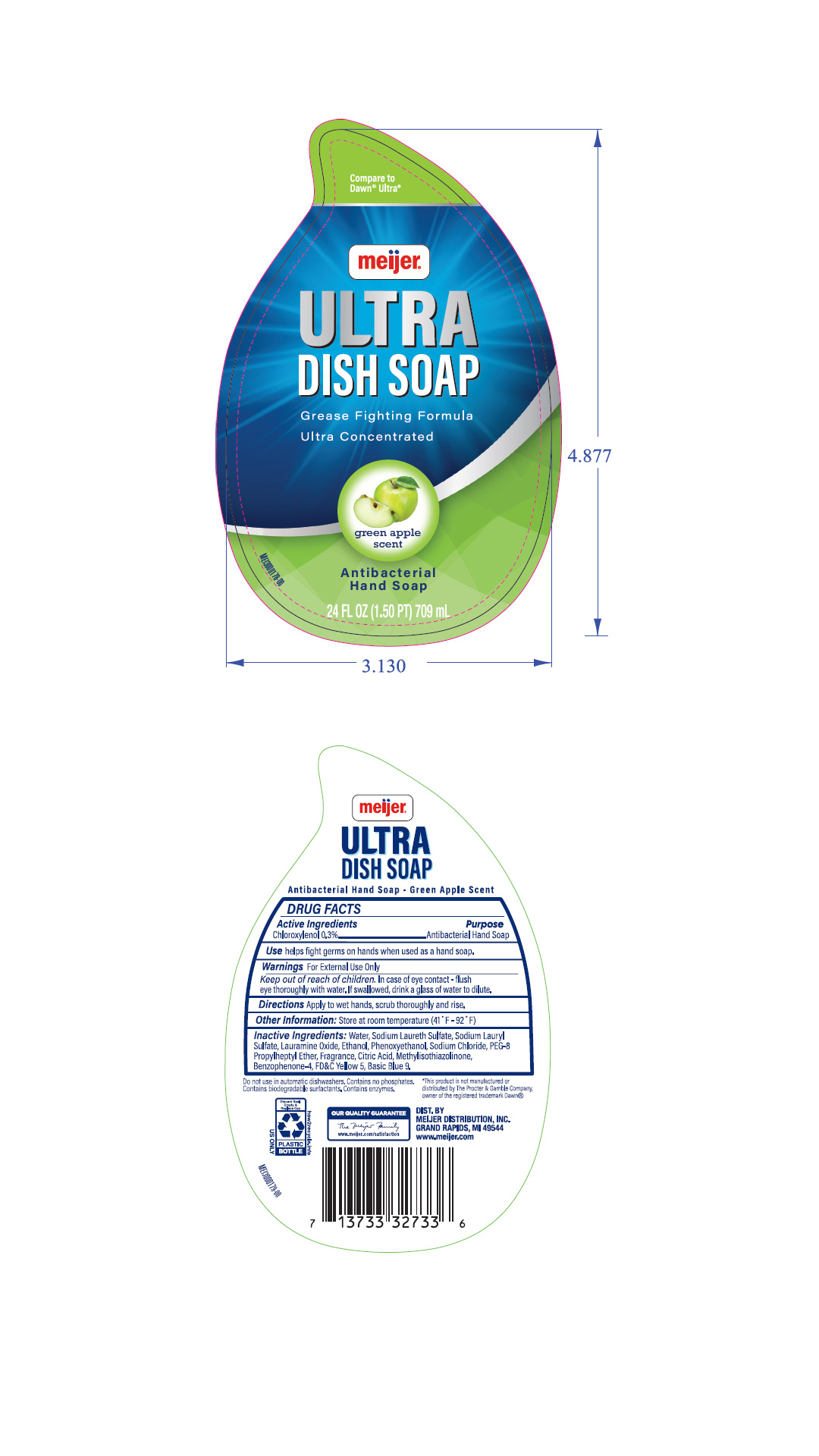 DRUG LABEL: Green Antibacterial Dish and HandSoap
NDC: 79481-0200 | Form: SOAP
Manufacturer: Meijer, Inc.
Category: otc | Type: HUMAN OTC DRUG LABEL
Date: 20240115

ACTIVE INGREDIENTS: CHLOROXYLENOL 30 mg/10 mL
INACTIVE INGREDIENTS: PPG-26; DECETH-8; SODIUM CHLORIDE; METHYLISOTHIAZOLINONE; FD&C YELLOW NO. 5; FD&C BLUE NO. 1; WATER; ALCOHOL; LAURAMINE OXIDE; SODIUM LAURETH-3 SULFATE; ACRYLIC ACID/SODIUM ACRYLATE COPOLYMER (1:1; 600 MPA.S AT 0.2%); SODIUM LAURYL SULFATE; PHENOXYETHANOL

Meijer Green Apple Antibacterial Dish and Hand Soap

PRINCIPAL DISPLAY PANEL - 709 mL Bottle Label

Compare to

Dawn ® Ultra*

meijer ®

Ultra

Dish Soap

Grease Fighting Formula

Ultra Concentrated

green apple scent

Antibacterial

Hand Soap

24 FL OZ (1.50 PT) 709 mL

MEI3000178-00

Directions

Apply to wet hands, scrub thoroughly and rinse.

Warnings

For External Use Only

Inactive ingredients:

Water, Sodium Laureth Sulfate, Sodium Lauryl Sulfate, Lauramine Oxide, Ethanol, Phenoxyethanol, Sodium Chloride, PEG-8 Propylheptyl Ether, Fragrance, Citric Acid, Methyl-4-isothiazolin-3-one, Benzophenone-4, FD&C Yellow 5 (CI19140), Basic Blue 9 (CI52015)

Indications and Usage:

Helps fight germs on hands when used as a hand soap.

Keep out of reach of children.

In case of eye contact - flush eye thoroughly with water. If swallowed, drink glass of water to dilute.

Use

helps fight germs on hands when used as a hand soap.

Do not use in automatic dish washers. Contains no phosphates.

Contains iodegradable surfactants. Contains enzymes.

*This product is not manufactured or

distributed by The Procter & Gamble Company,

owner of the registered trademark Dawn®

Active ingredients

Chloroxylenol 0.3%......................Antibacterial Hand Soap